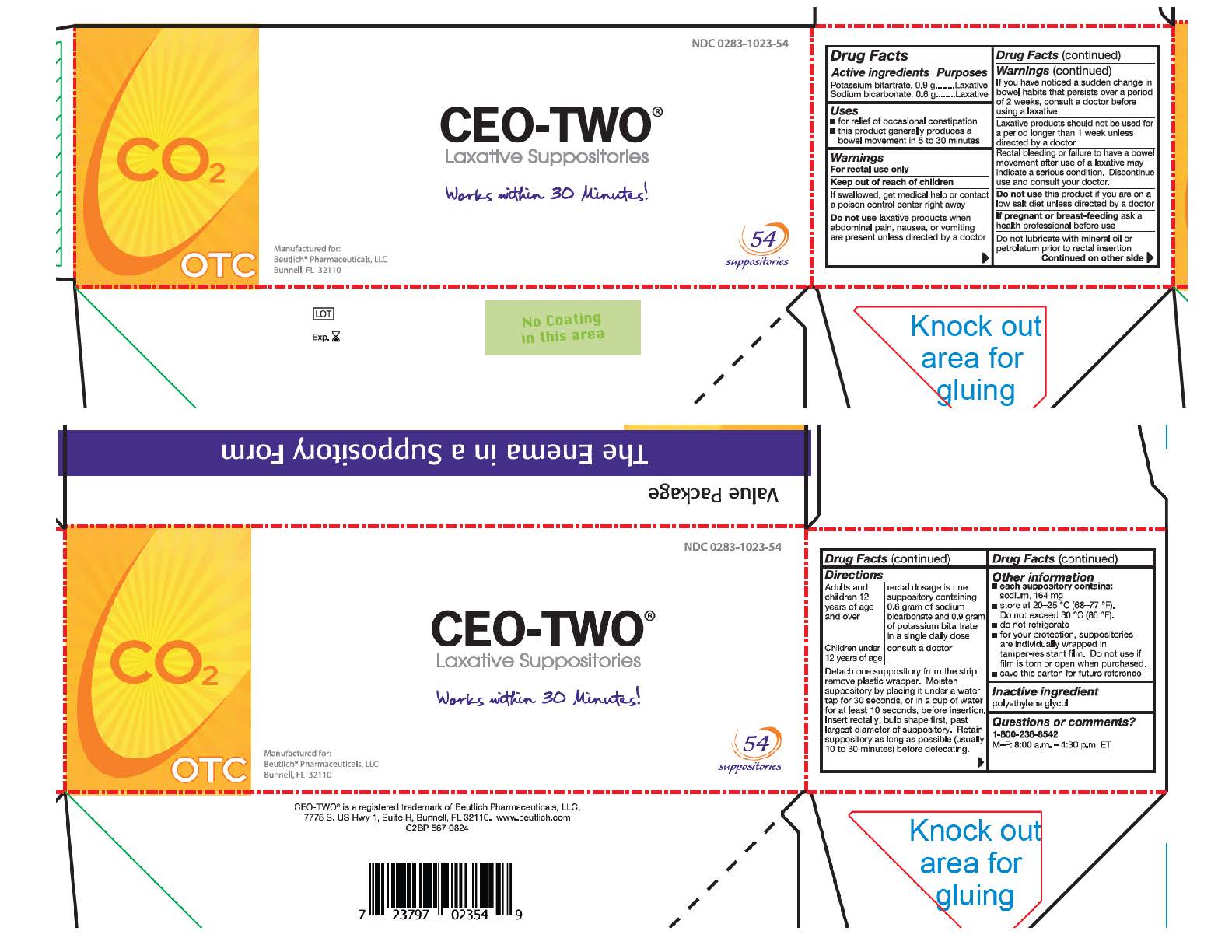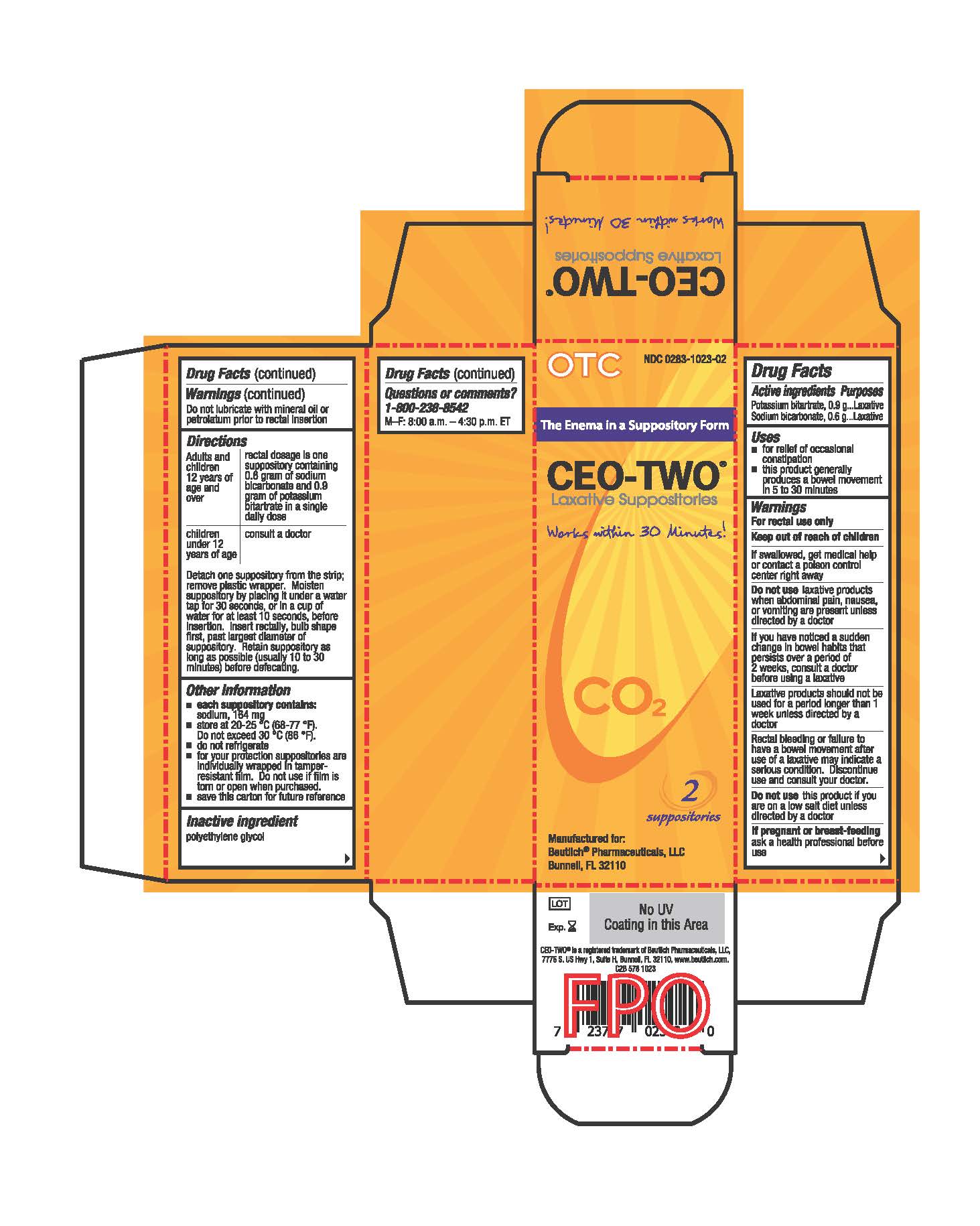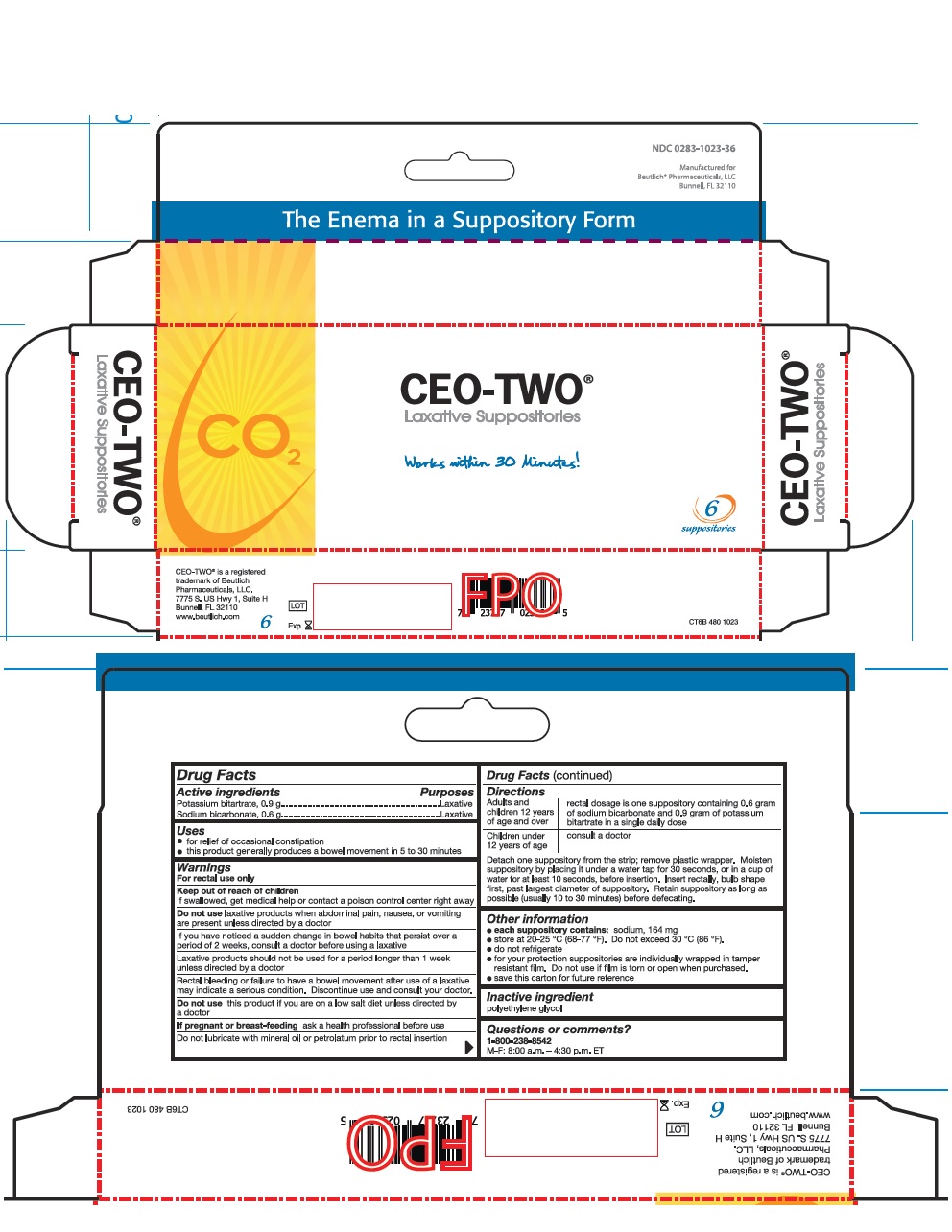 DRUG LABEL: CEO-TWO
NDC: 0283-1023 | Form: SUPPOSITORY
Manufacturer: Beutlich Pharmaceuticals, LLC
Category: otc | Type: HUMAN OTC DRUG LABEL
Date: 20251105

ACTIVE INGREDIENTS: POTASSIUM BITARTRATE 0.9 g/5.7 g; SODIUM BICARBONATE 0.6 g/5.7 g
INACTIVE INGREDIENTS: POLYETHYLENE GLYCOL 1450 4.2 g/5.7 g

CEO TWO

Active ingredients

Potassium bitartrate, 0.9 g

Sodium bicarbonate, 0.6 g

Purposes

Laxative

Uses

- for relief of occasional constipation
- this product generally produces a bowel movement in 5 to 30 minutes

Warnings

For rectal use only

Keep out of reach of children

If swallowed, get medical help or contact a poison control center right away

Do not use laxative products when abdominal pain, nausea, or vomiting are present unless directed by a doctor

Do not use this product if you are on a low salt diet unless directed by a doctor

Do not lubricate with mineral oil or petrolatum prior to rectal insertion

ASK DOCTOR

If you have noticed a sudden change in bowel habits that persists over a period of 2 weeks, consult a doctor before using a laxative

Laxative products should not be used for a period longer than 1 week unless directed by a doctor

STOP USE

Rectal bleeding or failure to have a bowel movement after use of a laxative may indicate a serious condition. Discontinue use and consult your doctor.

If pregnant or breast-feeding

ask a health professional before use

Directions

Adults and children 12 years of age and over: rectal dosage is one suppository containing 0.6 gram of sodium bicarbonate and 0.9 gram of potassium bitartrate in a single daily dose

Children under 12 years of age: consult a doctor

Detach one suppository from the strip; remove plastic wrapper. Moisten suppository by placing it under a water tap for 30 seconds, or in a cup of water for at least 10 seconds, before insertion. Insert rectally, bulb shape first, past largest diameter of suppository. Retain suppository as long as possible (usually 10 to 30 minutes) before defecating.

PATIENT COUNSELING INFORMATION

- each suppository contains: sodium, 164 mg

Other information

- store at 20-25 ºC (68-77 ºF). Do not exceed 30 ºC (86 ºF).
- do not refrigerate
- for your protection, suppositories are individually wrapped in tamper-resistant film. Do not use if film is torn or open when purchased.
- save this carton for future reference

Inactive ingredient

polyethylene glycol

Questions or comments?

1-800-238-8542

M-F: 8:00 a.m. - 4:30 p.m. ET

Prinicipal Display Panel - 54 count

CEO-TWO Laxative Suppositories

Box of 2:

Box of 6:

Box of 54: